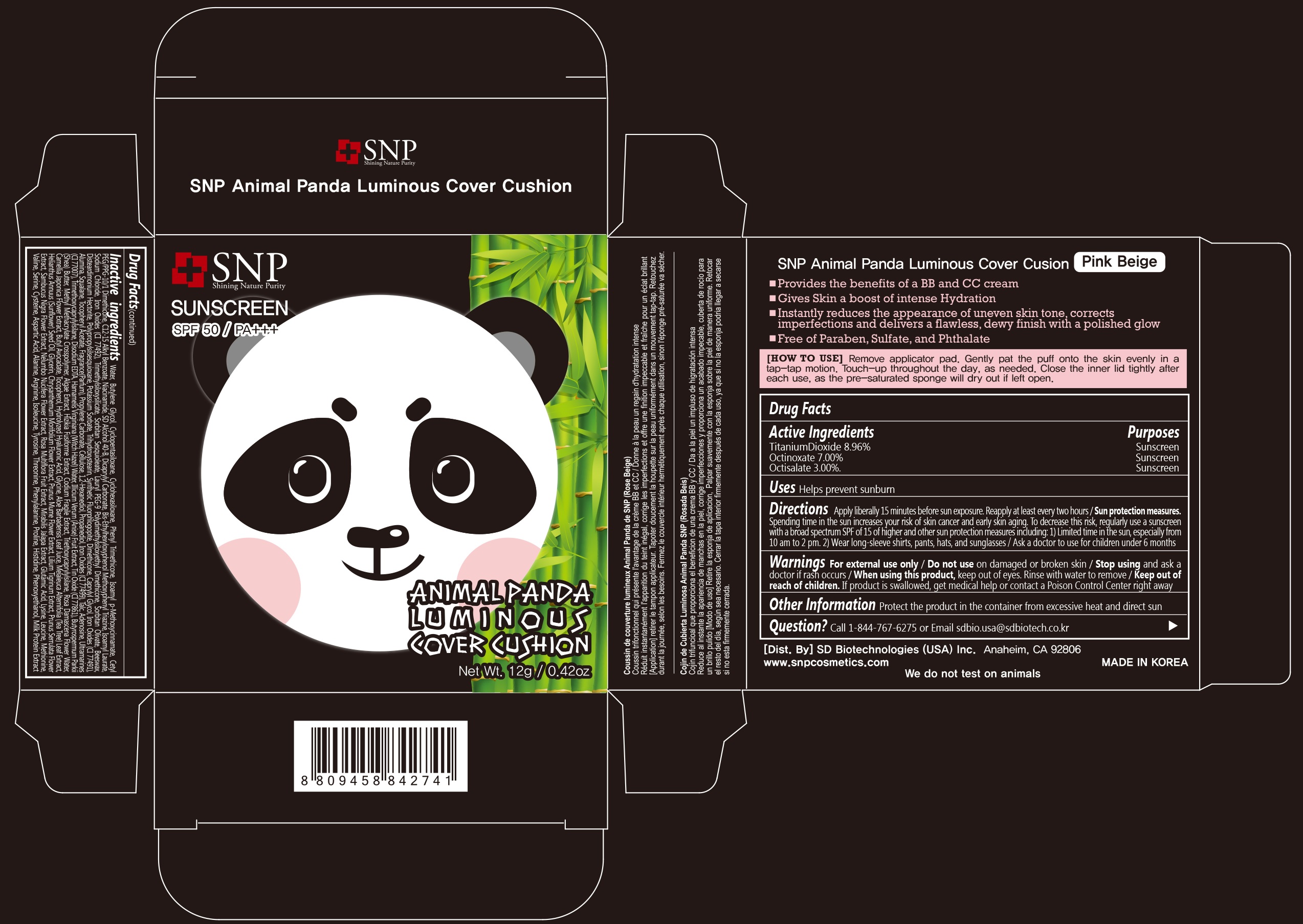 DRUG LABEL: SNP Animal Panda Luminous Cover Cushion
NDC: 70142-001 | Form: CREAM
Manufacturer: SD BIOTECHNOLOGIES CO., LTD
Category: otc | Type: HUMAN OTC DRUG LABEL
Date: 20161016

ACTIVE INGREDIENTS: TITANIUM DIOXIDE 1.0752 g/12 g; OCTINOXATE 0.84 g/12 g; OCTISALATE 0.36 g/12 g
INACTIVE INGREDIENTS: WATER; BUTYLENE GLYCOL; CYCLOMETHICONE 5; CYCLOMETHICONE 6; PHENYL TRIMETHICONE; AMILOXATE; CETYL PEG/PPG-10/1 DIMETHICONE (HLB 2); ALKYL (C12-15) BENZOATE; NIACINAMIDE; ALCOHOL; DICAPRYLYL CARBONATE; BEMOTRIZINOL; ISOAMYL LAURATE; SODIUM CHLORIDE; FERRIC OXIDE YELLOW; TRIMETHYLSILOXYSILICATE (M/Q 0.6-0.8); SORBITAN SESQUIOLEATE; LAURYL PEG-9 POLYDIMETHYLSILOXYETHYL DIMETHICONE; SORBITAN OLIVATE; YELLOW WAX; DISTEARDIMONIUM HECTORITE; POTASSIUM SORBATE; TRIHYDROXYSTEARIN; DIMETHICONE; CAPRYLYL GLYCOL; FERRIC OXIDE RED; ALUMINUM OXIDE; CERESIN; SQUALANE; .ALPHA.-TOCOPHEROL ACETATE; PROPYLENE CARBONATE; POWDERED CELLULOSE; 1,2-HEXANEDIOL; PROPANEDIOL; FERROSOFERRIC OXIDE; TALC; ADENOSINE; ULTRAMARINE BLUE; TRIMETHOXYCAPRYLYLSILANE; EDETATE DISODIUM; HAMAMELIS VIRGINIANA TOP WATER; STAR ANISE FRUIT; STANNIC OXIDE; SHEA BUTTER; PHYMATOLITHON CALCAREUM; SARGASSUM FUSIFORME; CODIUM FRAGILE; TRIETHOXYCAPRYLYLSILANE; ROSA DAMASCENA FLOWER OIL; CAMELLIA JAPONICA FLOWER; TOCOPHEROL; GLYCINE; ALOE VERA LEAF; MELALEUCA ALTERNIFOLIA LEAF; SUNFLOWER OIL; GLYCERIN; CHRYSANTHEMUM X MORIFOLIUM FLOWER; PRUNUS MUME FLOWER; LILIUM LANCIFOLIUM BULB; PRUNUS SERRULATA FLOWER; SAMBUCUS NIGRA FLOWER; NELUMBO NUCIFERA FLOWER; ROSA MULTIFLORA FRUIT; MIRABILIS JALAPA SEED; GLUTAMIC ACID; LYSINE; LEUCINE; METHIONINE; VALINE; SERINE; CYSTEINE; ASPARTIC ACID; ALANINE; ARGININE; ISOLEUCINE; TYROSINE; THREONINE; PHENYLALANINE; PROLINE; HISTIDINE; PHENOXYETHANOL; CASEIN

Drug Facts

ACTIVE INGREDIENT

Titanium Dioxide 8.96%
Octinoxate 7.00%
Octisalate 3.00%

PURPOSE

Sunscreen

INDICATIONS AND USAGE

Helps prevent sunburn

DOSAGE AND ADMINISTRATION

Apply liberally 15 minutes before sun exposure. Reapply at least every two hours

Sun protection measures. Spending time in the sun increases your risk of skin cancer and early skin aging. To decrease this risk, regularly use a sunscreen with a broad spectrum SPF of 15 of higher and other sun protection measures including: 1) Limited time in the sun, especially from 10 am to 2 pm. 2) Wear long-sleeve shirts, pants, hats, and sunglasses

Ask a doctor to use for children under 6 months

WARNINGS

For external use only

Do not use on damaged or broken skin

When using this product, keep out of eyes. Rinse with water to remove.

Stop using and ask a doctor if rash occurs.

KEEP OUT OF REACH OF CHILDREN

Keep out of reach of the children. If product is swallowed, get medical help or contact a poison control center right away.

INACTIVE INGREDIENT

Water, Butylene Glycol, Cyclopentasiloxane, Cyclohexasiloxane, Phenyl Trimethicone, Isoamyl p-Methoxycinnamate, Cetyl PEG/PPG-10/1 Dimethicone, C12-15 Alkyl Benzoate, Niacinamide, SD Alcohol 40-B, Dicaprylyl Carbonate, Bis-Ethylhexyloxyphenol Methoxyphenyl Triazine, Isoamyl Laurate, Sodium Chloride, Iron Oxides (CI 77492), Trimethylsiloxysilicate, Sorbitan Sesquioleate, Lauryl PEG-9 Polydimethylsiloxyethyl Dimethicone, Sorbitan Olivate, Beeswax, Disteardimonium Hectorite, Polypropylsilsesquioxane, Potassium Sorbate, Trihydroxystearin, Synthetic Fluorphlogopite, Dimethicone, Caprylyl Glycol, Iron Oxides (CI 77491), Alumina, Squalane, Tocopheryl Acetate, Fragrance(Parfum), Propylene Carbonate, Cellulose, 1,2-Hexanediol, Propanediol, Iron Oxides (CI 77499), Talc, Adenosine, Ultramarines (CI 77007), Trimethoxycaprylylsilane, Disodium EDTA, Hamamelis Virginiana (Witch Hazel) Water, Illicium Verum (Anise) Fruit Extract, Tin Oxide (CI 77861), Butyrospermum Parkii (Shea) Butter, Methyl Methacrylate Crosspolymer, Algae Extract, Hizikia Fusiforme Extract, Codium Fragile Extract, Triethoxycaprylylsilane, Rosa Damascena Flower Water, Camellia Japonica Flower Extract, Butyl Avocadate, Tocopherol, Hydrolyzed Hyaluronic Acid, Glycine, Aloe Barbadensis Leaf Juice, Melaleuca Alternifolia (Tea Tree) Leaf Extract, Helianthus Annuus (Sunflower) Seed Oil, Glycerin, Chrysanthemum Morifolium Flower Extract, Prunus Mume Flower Extract, Lilium Tigrinum Extract, Prunus Serrulata Flower Extract, Sambucus Nigra Flower Extract, Nelumbo Nucifera Flower Extract, Rosa Multiflora Fruit Extract, Mirabilis Jalapa Extract, Glutamic Acid, Lysine, Leucine, Methionine, Valine, Serine, Cysteine, Aspartic Acid, Alanine, Arginine, Isoleucine, Tyrosine, Threonine, Phenylalanine, Proline, Histidine, Phenoxyethanol, Milk Protein Extract

OTHER SAFETY INFORMATION

Protect the product in the container from excessive heat and direct sun

QUESTIONS

Call 1-844-767-6275 or Email sdbio.usa@sdbiotech.co.kr